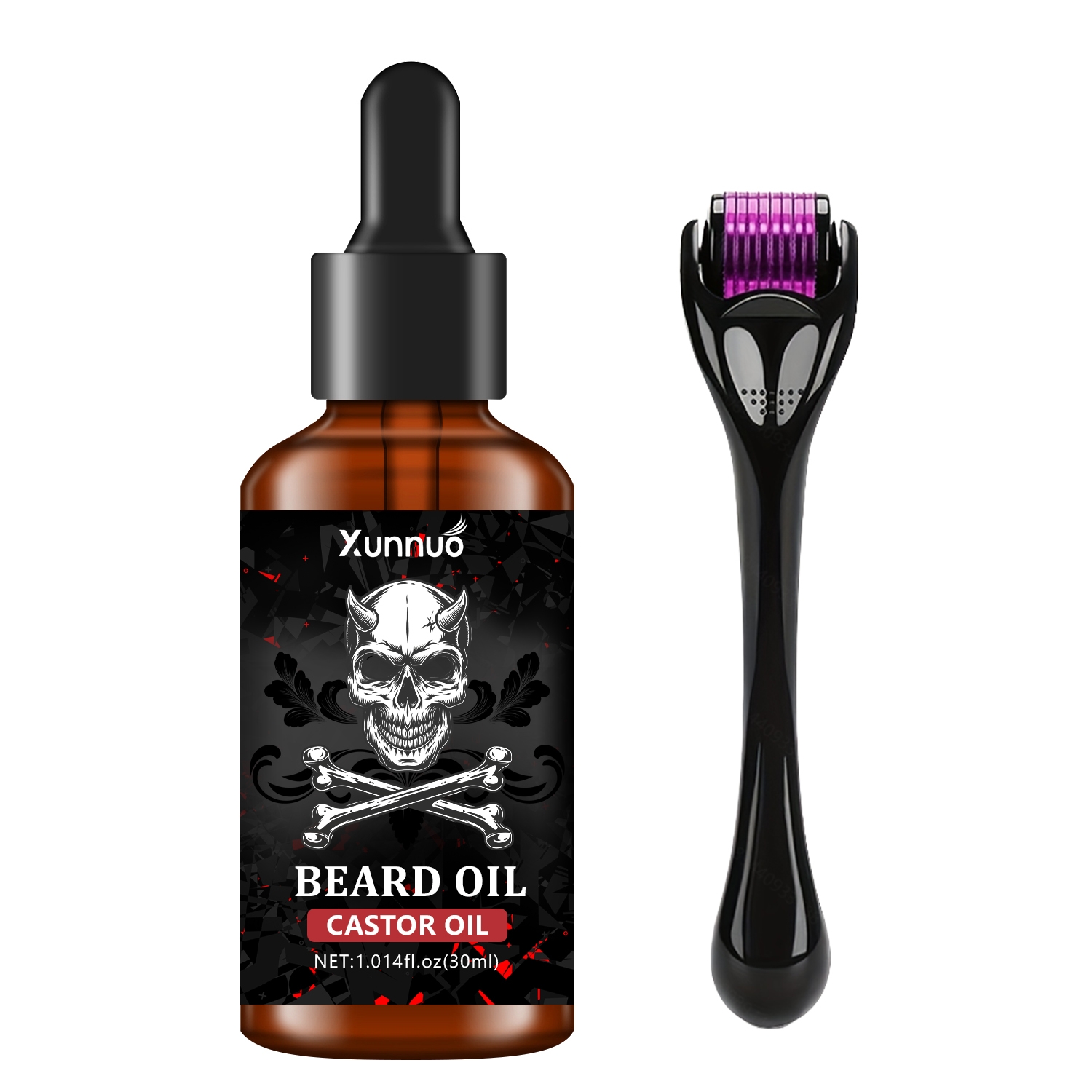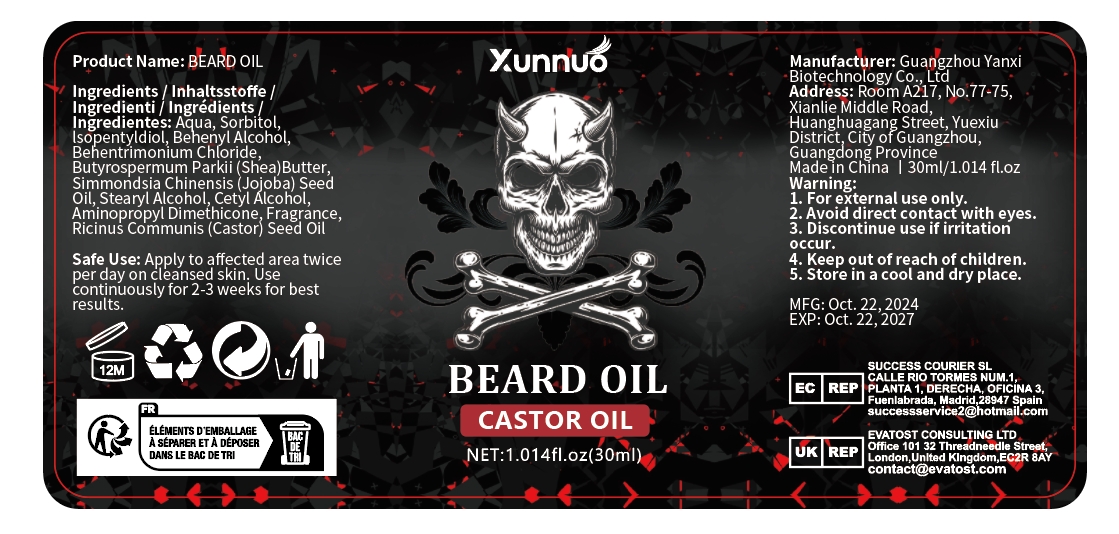 DRUG LABEL: beard oil
NDC: 84025-265 | Form: LIQUID
Manufacturer: Guangzhou Yanxi Biotechnology Co., Ltd
Category: otc | Type: HUMAN OTC DRUG LABEL
Date: 20241118

ACTIVE INGREDIENTS: ISOPENTYLDIOL 1 mg/30 mL; SORBITOL 2 mg/30 mL
INACTIVE INGREDIENTS: WATER

DOSAGE AND ADMINISTRATION

Apply to affected area twice per day on cleansed skin.

WARNINGS

keep out of children

INACTIVE INGREDIENT

Aqua

INDICATIONS AND USAGE

For daily skin care

Keep out of children

PURPOSE

Moisturizing skin